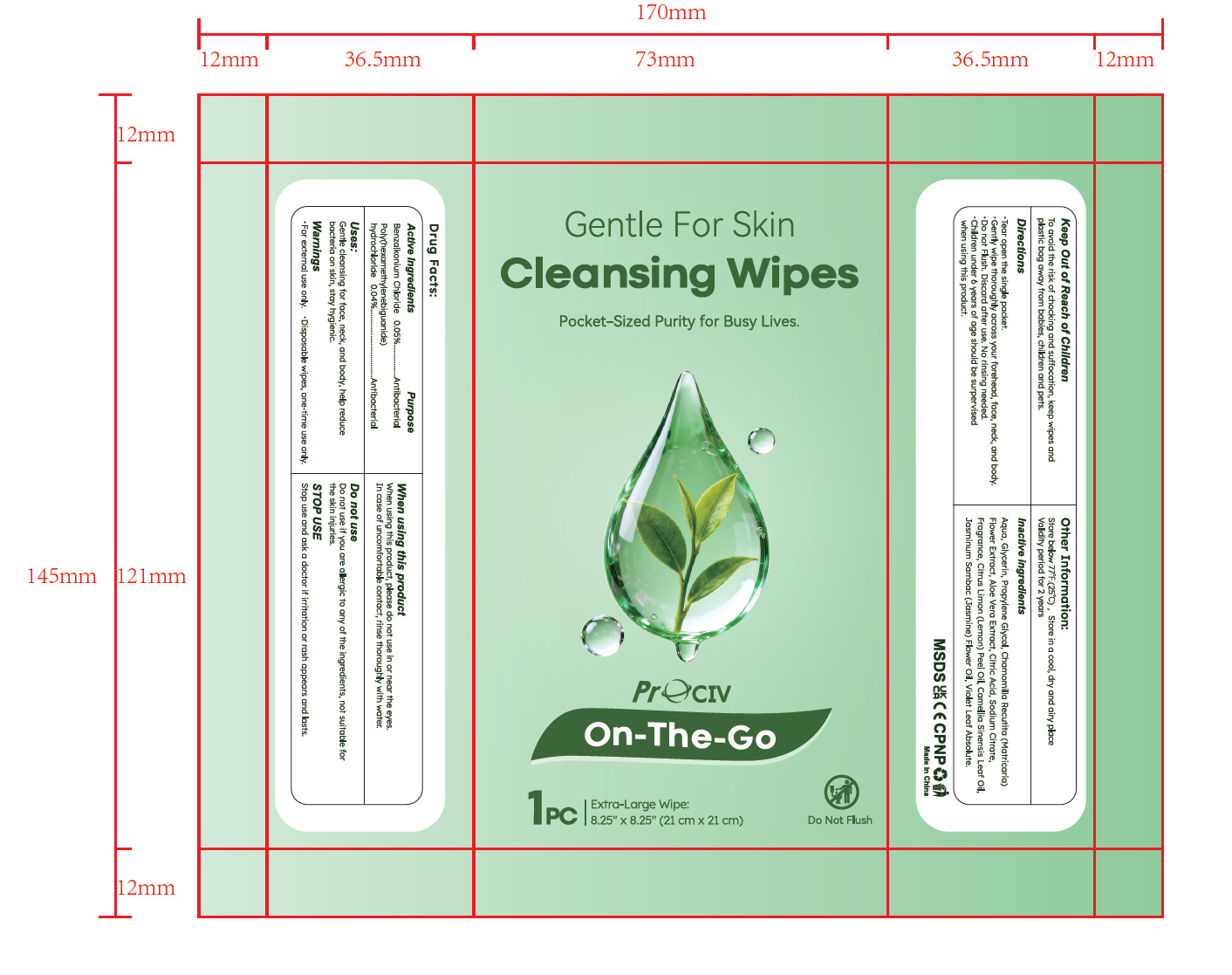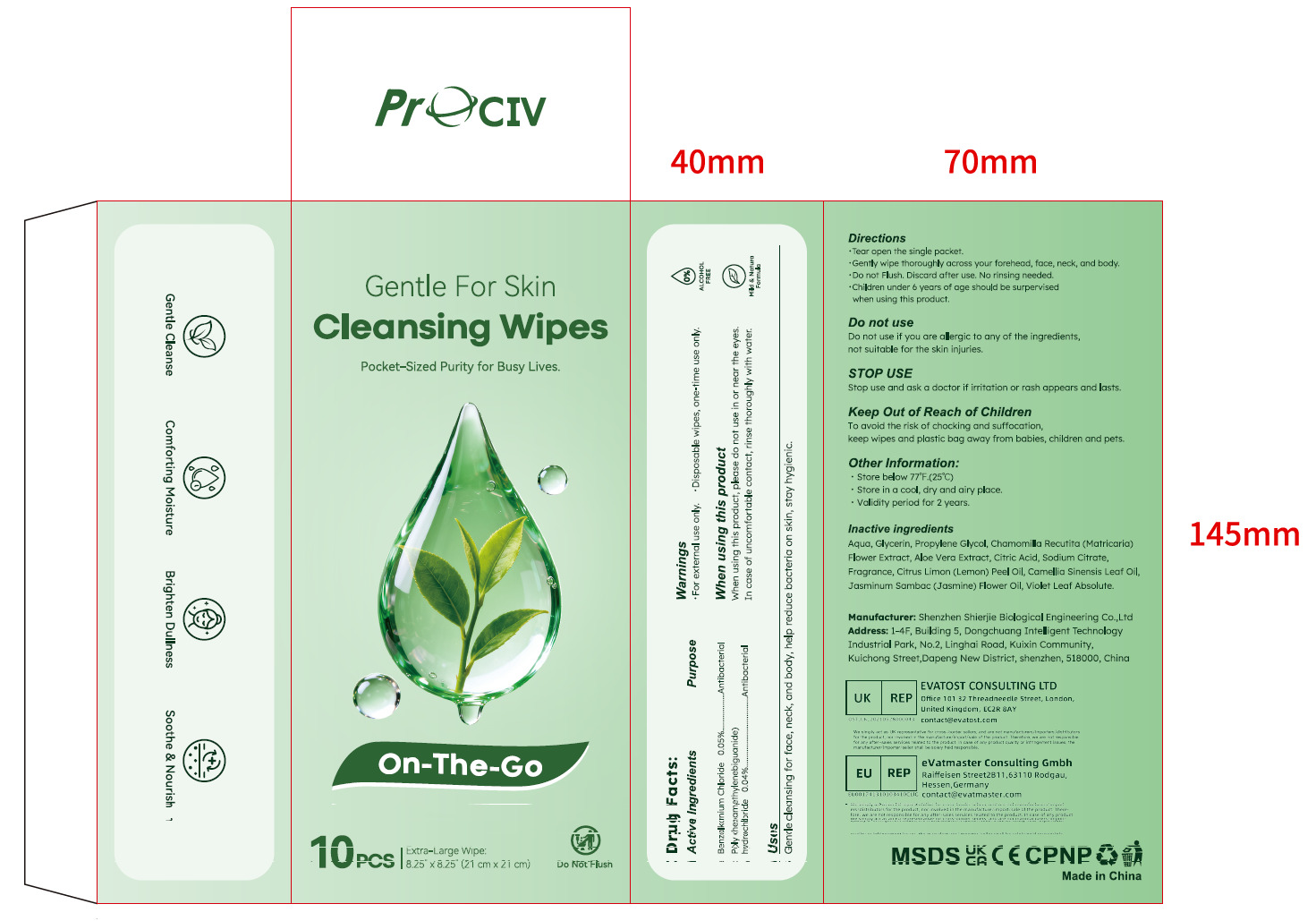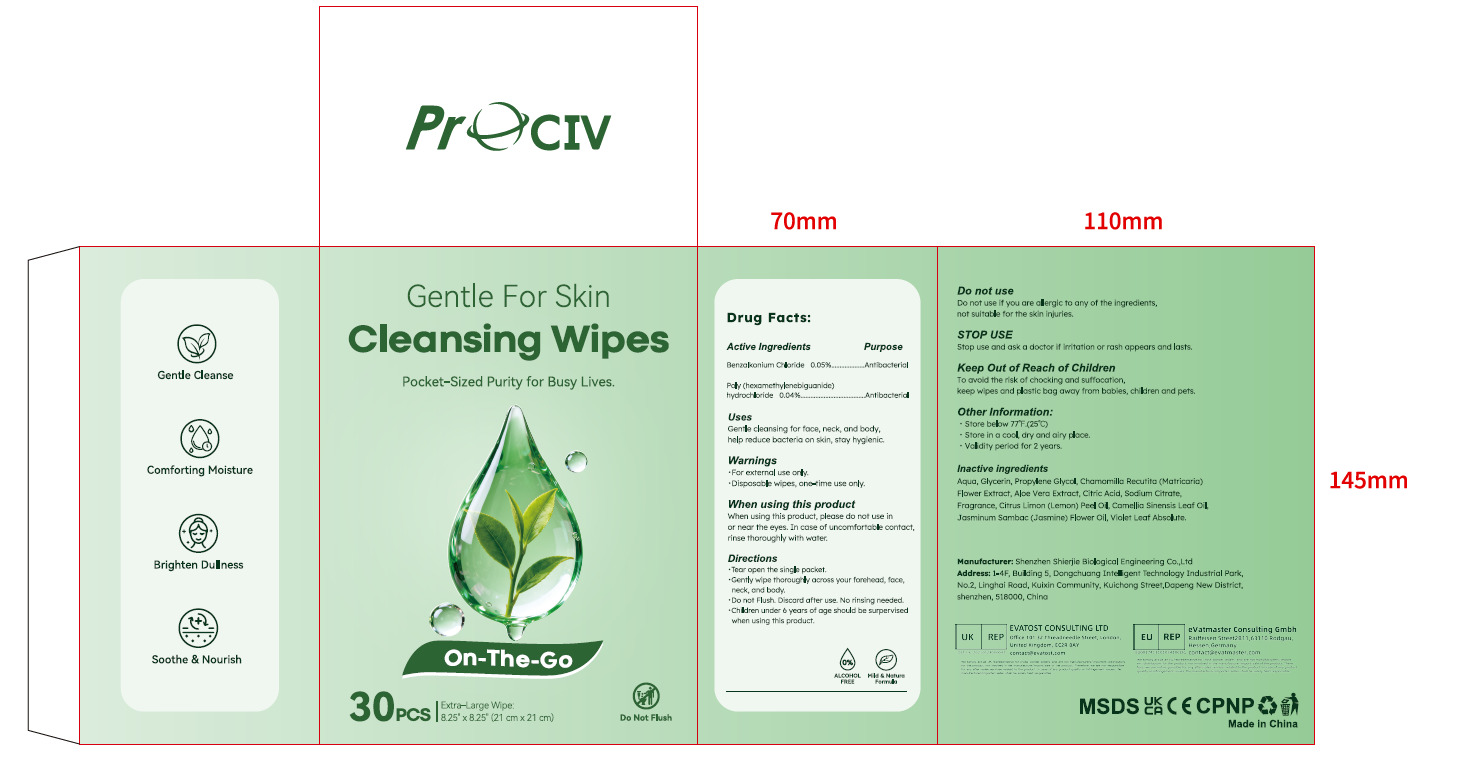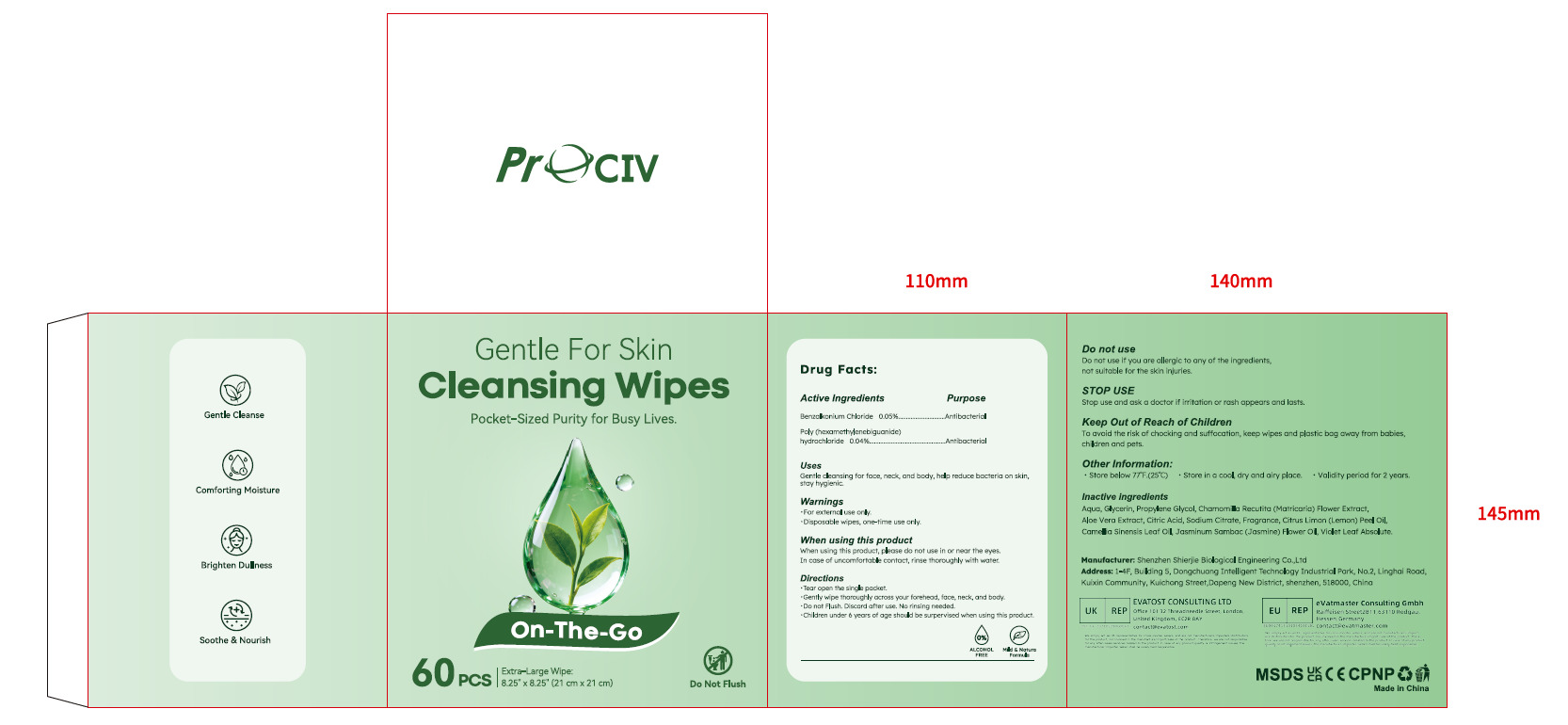 DRUG LABEL: Cleansing Wipes
NDC: 43116-047 | Form: CLOTH
Manufacturer: Shenzhen Shierjie Biological Engineering Co., LTD
Category: otc | Type: HUMAN OTC DRUG LABEL
Date: 20251117

ACTIVE INGREDIENTS: POLIHEXANIDE HYDROCHLORIDE 0.04 U/100 U; BENZALKONIUM CHLORIDE 0.05 U/100 U
INACTIVE INGREDIENTS: FRAGRANCE GREEN FLORAL ORC2000883; CITRUS LIMON (LEMON) PEEL OIL; JASMINUM SAMBAC (JASMINE) FLOWER OIL; CITRIC ACID; VIOLA ODORATA OIL; SODIUM CITRATE; AQUA; GLYCERIN; PROPYLENE GLYCOL; CHAMOMILE; ALOE VERA LEAF; CAMELLIA SINENSIS LEAF OIL

43116-047

Active Ingredient

Benzalkonium Chloride 0.05%.
Poly (hexamethylenebiguanide) hydrochloride 0.04%

Purpose

Antibacterial

Use

Gentle cleansinng for face, neck, and body, help reduce bacteria on skin, stay hygienic

Warnings

●For external use only.
●Disposable wipes, one-time use only.

Do not use if you are allergic to any of the ingredients, not suitable for the skin injuries.

When Using

When using this product, please do not use in or near the eyes.
In case of uncomfortable contact, rinse thoroughly with water.

Stop Use

Stop use and ask a doctor if irritation or rash appears and lasts.

Keep Oot Of Reach Of Children

To avoid the risk of chocking and suffocation, keep wipes and plastic bag away from babies, children and pets.

Directions

●Tear open the single packet.
●Gently wipe thoroughly across your forehead, face, neck, and body.
●Do not Flush. Discard after use. No rinsing needed.
●Children under 6 years of age should be surpervised when using this product.

Other information

● Store below 77°F.(25"C)
● Store in a cool, dry and airy place.

● Validity period for 2 years.

Inactive ingredients

Aqua, Glycerin, Propylene Glycol, Chamomilla Recutita (Matricaria) Flower Extract,
Aloe Vera Extract, Citric Acid, Sodium Citrate, Fragrance, Citrus Limon (Lemon) Peel Oil,
Camellia Sinensis Leaf Oil, Jasminum Sambac (Jasmine) Flower Oil, Violet Leaf Absolute.